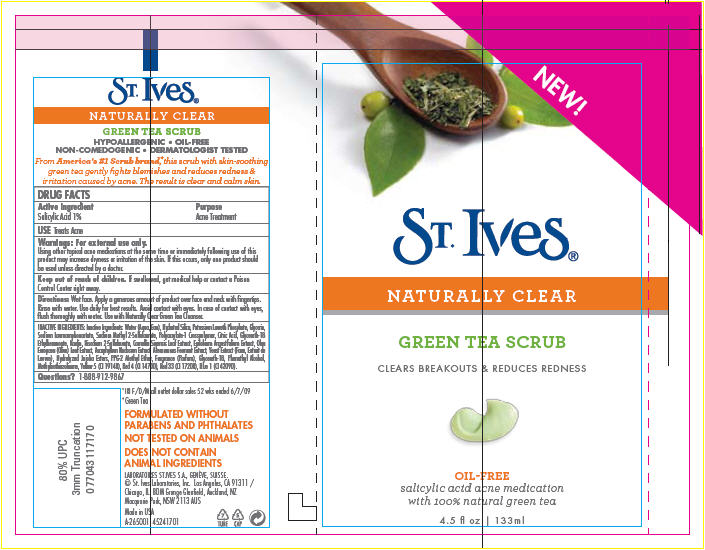 DRUG LABEL: St. Ives 
NDC: 12488-0300 | Form: SOAP
Manufacturer: Alberto-Culver USA Inc.
Category: otc | Type: HUMAN OTC DRUG LABEL
Date: 20100108

ACTIVE INGREDIENTS: Salicylic Acid 0.01 mL/1 mL
INACTIVE INGREDIENTS: Water; D&C Red No. 33; Fd&C Red No. 4; Fd&C Blue No. 1; Kaolin; Citric Acid Monohydrate; Glycerin; Methylisothiazolinone; Phenethyl Alcohol; Green Tea Leaf

ST. Ives®
NATURALLY CLEAR
GREEN TEA SCRUB

DRUG FACTS

Active Ingredient

Salicylic Acid 1%

Purpose

Acne Treatment

USE

Treats Acne

Warnings

For external use only.

WHEN USING

Using other topical acne medications at the same time or immediately following use of this product may increase dryness or irritation of the skin. If this occurs, only one product should be used unless directed by a doctor.

Keep out of reach of children. If swallowed, get medical help or contact a Poison Control Center right away.

Directions

Wet face. Apply a generous amount of product over face and neck with fingertips. Rinse with water. Use daily for best results. Avoid contact with eyes. In case of contact with eyes, flush thoroughly with water. Use with Naturally Clear Green Tea Cleanser.

INACTIVE INGREDIENTS

Inactive Ingredients: Water (Aqua, Eau), Hydrated Silica, Potassium Laureth Phosphate, Glycerin, Sodium Lauroamphoacetate, Sodium Methyl 2-Sulfolaurate, Polyacrylate-1 Crosspolymer, Citric Acid, Glycereth-18 Ethylhexanoate, Kaolin, Disodium 2-Sulfolaurate, Camellia Sinensis Leaf Extract, Epilobium Angustifolium Extract, Olea Europaea (Olive) Leaf Extract, Ascophyllum Nodosum Extract, Alteromonas Ferment Extract, Yeast Extract (Faex, Extrait de Levure), Hydrolyzed Jojoba Esters, PPG-2 Methyl Ether, Fragrance (Parfum), Glycereth-18, Phenethyl Alcohol, Methylisothiazolinone, Yellow 5 (CI 19140), Red 4 (CI 14700), Red 33 (CI 17200), Blue 1 (CI 42090).

Questions?

1-888-912-9867

PRINCIPAL DISPLAY PANEL - 133 mL Bottle Label

NEW!

ST. Ives®

NATURALLY CLEAR

GREEN TEA SCRUB

CLEARS BREAKOUTS & REDUCES REDNESS

OIL-FREE
salicylic acid acne medication
with 100% natural green tea

4.5 fl oz | 133ml